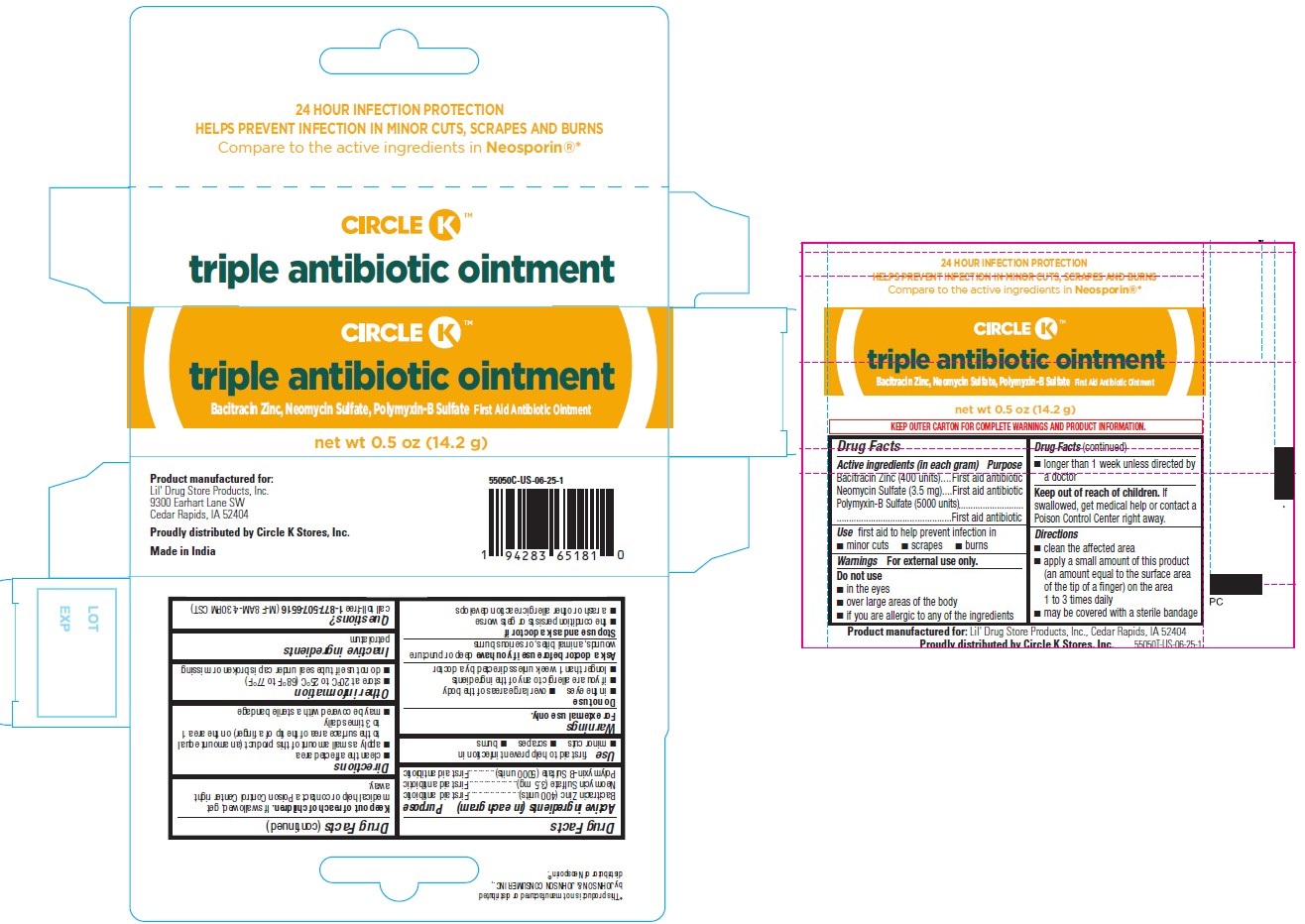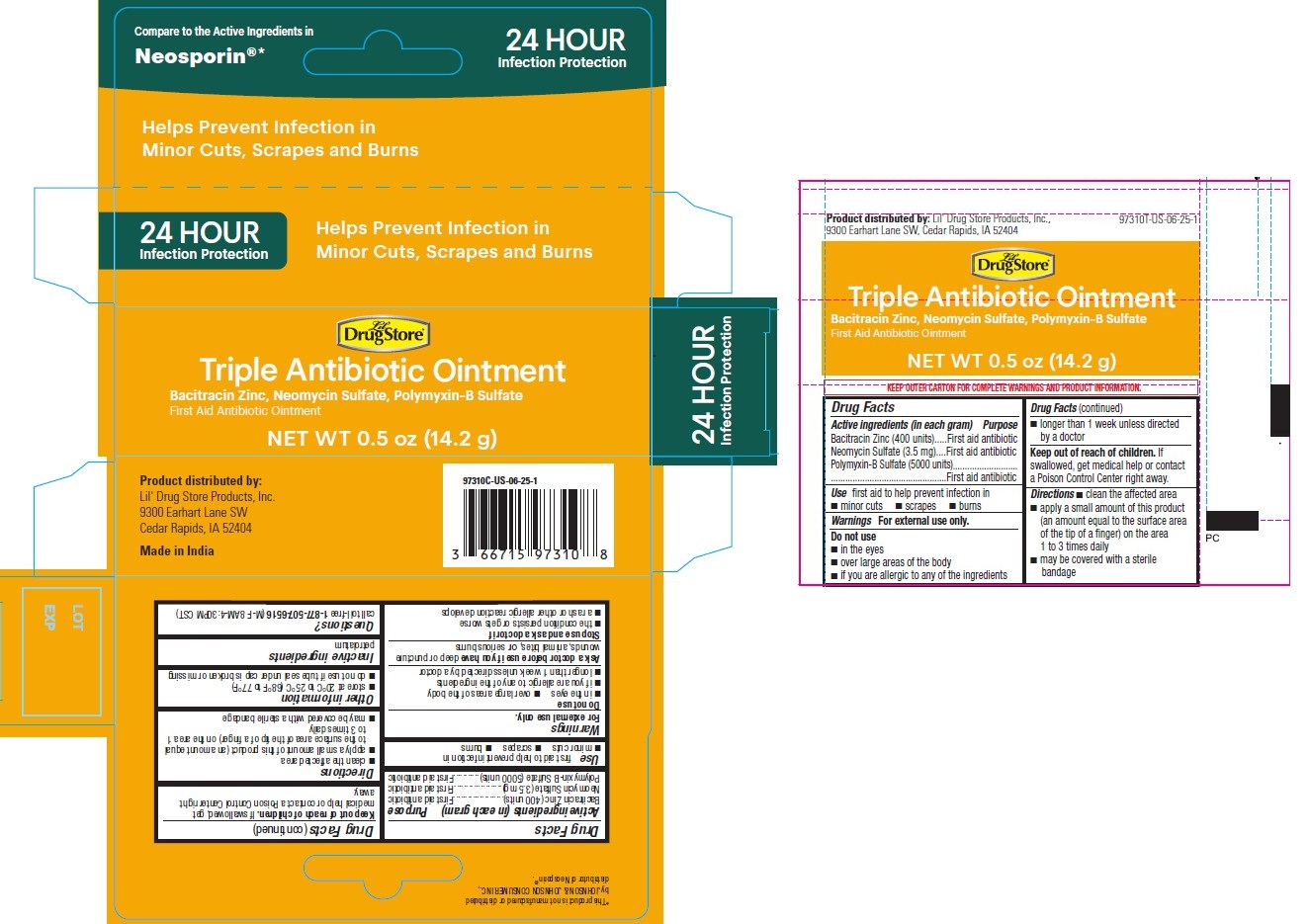 DRUG LABEL: Triple Antibiotic Ointment, Lil Drug Store Products
NDC: 66715-9531 | Form: OINTMENT
Manufacturer: Lil' Drug Store Products, Inc.
Category: otc | Type: HUMAN OTC DRUG LABEL
Date: 20251201

ACTIVE INGREDIENTS: NEOMYCIN SULFATE 3.5 mg/1 g; BACITRACIN ZINC 400 [iU]/1 g; POLYMYXIN B SULFATE 5000 [iU]/1 g
INACTIVE INGREDIENTS: PETROLATUM

Triple Antibiotic Ointment

Drug Facts

Active ingredients

Active ingredients (in each gram)

Bacitracin Zinc (400 units)

Neomycin Sulfate (3.5 mg)

Polymixin-B Sulfate (5000 units)

Purpose

First aid antibiotic

First aid antibiotic

First aid antibiotic

Use

First aid to help prevent infection in

- minor cuts
- scrapes
- burns

Warnings

For external use only.

Do not use

- in the eyes
- over large areas of the body
- if you are allergic to any of the ingredients
- longer than 1 week unless directed by a docto

Ask a doctor before use if you have deep or puncture wounds, animal bites, or serious burns

Stop use and ask a doctor if

- the condition persists or gets worse
- a rash or other allergic reaction develops

Keep out of reach of children. If swallowed, get medical help or contact a Poison Control Center right away.

Directions

- clean the affected area
- apply a small amount of this product (an amount equal to the surface area of the tip of a finger) on the area 1 to 3 times daily
- may be covered with a sterile bandage

Other information

- store at 20°C to 25°C (68°F to 77°F)
- do not use if tube seal under cap is broken or missing

Inactive ingredients

petrolatum

Questions?

call toll-free 1-877-507-6516 (M-F 8AM-4:30PM CST)

Triple Antibiotic Ointment, Lil' Drug Store®

Compare to the Active Ingredients in
Neosporin®*

24 HOUR

Infection Protection

Helps Prevent Infection in
Minor Cuts, Scrapes and Burns

[Lil' Drug Store logo]

Triple Antibiotic Ointment

Bacitracin Zinc, Neomycin Sulfate, Polymyxin-B Sulfate
First Aid Antibiotic Ointment

NET WT 0.5 oz (14.2 g)

Triple Antibiotic Ointment, Circle K™

24 HOUR INFECTION PROTECTION
HELPS PREVENT INFECTION IN MINOR CUTS, SCRAPES AND BURNS
Compare to the active ingredients in Neosporin®*

[Circle K logo]

triple antibiotic ointment

Bacitracin Zinc, Neomycin Sulfate, Polymyxin-B Sulfate First Aid Antibiotic Ointment

net wt 0.5 oz (14.2 g)